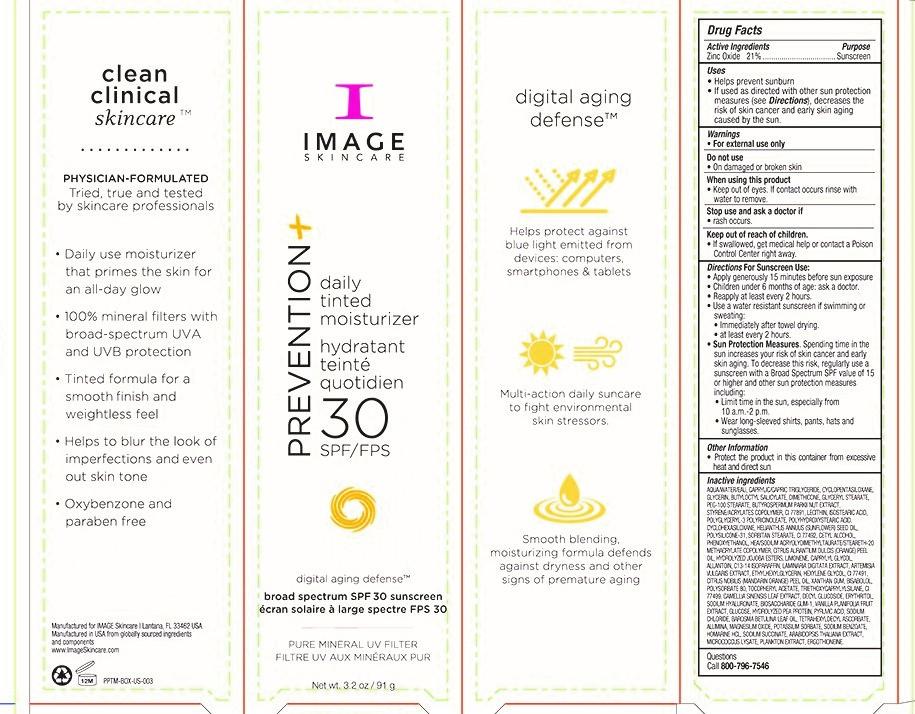 DRUG LABEL: Prevention Plus Daily Tinted Moisturizer SPF 30
NDC: 62742-4170 | Form: CREAM
Manufacturer: Allure Labs Inc
Category: otc | Type: HUMAN OTC DRUG LABEL
Date: 20190917

ACTIVE INGREDIENTS: ZINC OXIDE 210 mg/1 g
INACTIVE INGREDIENTS: WATER; MEDIUM-CHAIN TRIGLYCERIDES; CYCLOMETHICONE 5; GLYCERIN; BUTYLOCTYL SALICYLATE; DIMETHICONE; GLYCERYL STEARATE CITRATE; PEG-100 STEARATE; SHEA BUTTER; STYRENE/ACRYLAMIDE COPOLYMER (500000 MW); TITANIUM DIOXIDE; LECITHIN, SOYBEAN; ISOSTEARIC ACID; POLYGLYCERYL-3 RICINOLEATE; POLYHYDROXYSTEARIC ACID (2300 MW); CYCLOMETHICONE 6; SUNFLOWER OIL; POLYSILICONE-15; SORBITAN MONOSTEARATE; FERRIC OXIDE YELLOW; CETYL ALCOHOL; PHENOXYETHANOL; HYDROXYETHYL ACRYLATE/SODIUM ACRYLOYLDIMETHYL TAURATE COPOLYMER (100000 MPA.S AT 1.5%); STEARETH-20 METHACRYLATE; CITRUS AURANTIUM FRUIT OIL; HYDROLYZED JOJOBA ESTERS (ACID FORM); LIMONENE, (+)-; CAPRYLYL GLYCOL; ALLANTOIN; C13-14 ISOPARAFFIN; LAMINARIA DIGITATA; ARTEMISIA VULGARIS TOP OIL; ETHYLHEXYLGLYCERIN; HEXYLENE GLYCOL; FERRIC OXIDE RED; MANDARIN OIL; XANTHAN GUM; LEVOMENOL; POLYSORBATE 80; .ALPHA.-TOCOPHEROL ACETATE, DL-; TRIETHOXYCAPRYLYLSILANE; FERROSOFERRIC OXIDE; GREEN TEA LEAF; DECYL GLUCOSIDE; ERYTHRITOL; HYALURONATE SODIUM; BIOSACCHARIDE GUM-1; VANILLA; ANHYDROUS DEXTROSE; PEA PROTEIN; PYRUVIC ACID; SODIUM CHLORIDE; AGATHOSMA BETULINA LEAF OIL; TETRAHEXYLDECYL ASCORBATE; ALUMINUM OXIDE; MAGNESIUM OXIDE; POTASSIUM SORBATE; SODIUM BENZOATE; HOMARINE HYDROCHLORIDE; SODIUM SUCCINATE ANHYDROUS; ARABIDOPSIS THALIANA; MICROCOCCUS LUTEUS; ANACYSTIS NIDULANS; ERGOTHIONEINE

DRUG FACTS

Active Ingredients:

Zinc Oxide 21.0%

Purpose: Sunscreen

Uses:

- Helps prevent sunburn.
- If used as directed with other sun protection measures, decreases the risk of skin cancer and early skin aging caused by the sun.

WARNINGS AND PRECAUTIONS

Warning: For external use only.

Do not use: on damaged or broken skin.

When using this products:

- Keep out of eyes.If contact occurs rinse with water to remove.

Stop use and ask a doctor: If rash occurs.

Keep out of reach of children:

- If swallowed, get medical help or contact a Poison Control Center right away.

DOSAGE AND ADMINISTRATION

Directions For Sunscreen Use:

- Apply generously 15 minutes before sun exposure.
- Children under 6 months of age: ask a doctor.
- Reapply at least every 2 hours.
- Use a water resistant sunscreen if swimming or sweating.
- Immediatly after towel drying.
- at least every 2 hours.
- Sun protection measures.Spending time in the sun increase your risk of skin cancer and early skin aging. To decrease this risk, regularly use a sunscreen with a Broad Spectrum SPF value of 15 or higher and other sun protection measures including:
- limit time in the sun, especially from 10 a.m. - 2 p.m.
- wear long-sleeved shirts, pants, hats and sunglasses.

OTHER SAFETY INFORMATION

Protect the product in this container from excessive heat and direct sun.

INACTIVE INGREDIENT

Inactive Ingredients: Aqua/Water/EAU, Caprylyc/Capric Triglyceride, Cyclopentasiloxane, Glycerin, Butyloctyl Salicylate, Dimethicone, Glyceryl Stearate, PEG-100 Stearate, Butyrospermum Parkii Nut Extract, Styrene/Acrylates Copolymer, Cl 77891, Lecithin, Isostearic Acid, Polyglyceryl-3 Polyricinoleate, Polyhydroxystearic Acid, Cyclohexasiloxane, Helianthus Annus (Sunflower) seed oil, Polysilicone-31, Sorbitan Stearate, Cl 77492, Cetyl Alcohol, Phenoxyethanol, HEA/Sodium Acryolydimethyltaurate/Steareth-20 Methacrylate Copolymer, Citrus Aurantium Dulcis (Orange) peel oil, Hydrolyzed jojoba esters, Limonene, Caprylyl Glycol, Allantoin, C13-14 Isoparaffin, Laminaria Digitata Extract, Artemisia Vulgaris Extract, Ethylhexylglycerin, Hexylene Glycol, Cl 77491, Citrus Nobilis (Mandarin Orange) Peel Oil, Xanthan gum, Bisabolol, Polysorbate 80, Tocopheryl Acetate, Triethoxycaprylylsilane, Cl 77499, Camellia Sinensis Leaf Extract, Decyl Glucoside, Erythritol, Sodium Hyaluronate, Biosaccharide Gum-1, Vanilla Planifolia Fruit Extract, Glucose, Hydrolyzed Pea Protein, Pyruvic Acid, Sodium Chloride, Barosma Betulina Leaf Oil, Tetrahexyldecyl ascorbate, Alumina, Magnesium Oxide, Potassium Sorbate, Sodium Benzoate, Homarine HCL, Sodium Succinate, Arabidopsis Thaliana Extract, Micrococcus Lysate, Plankton Extract, Ergothioneine.

PACKAGE LABEL

Manufactured for IMAGE Skincare, Lantana, FL 33462 USA

Manufactured in USA from globally sourced ingredients and components

www.ImageSkincare.com

QUESTIONS

Call 800-796-7546